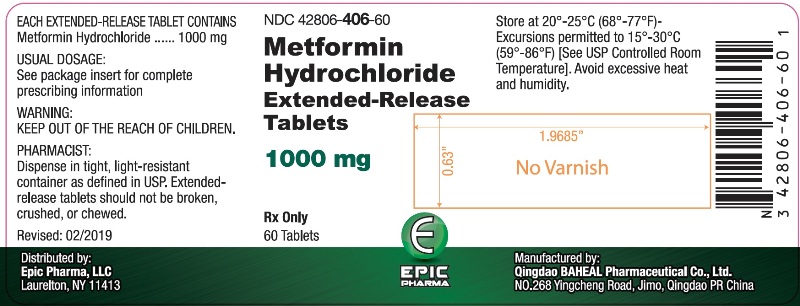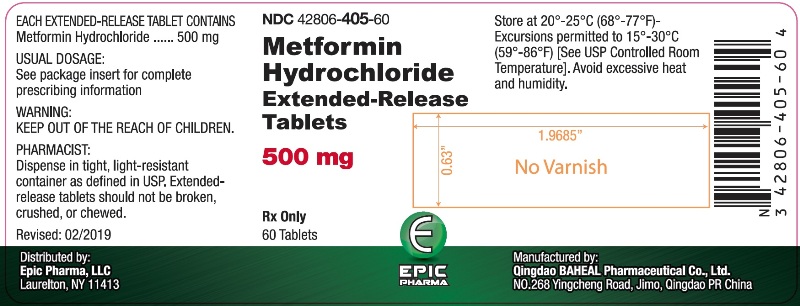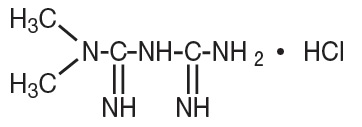 DRUG LABEL: metformin hydrochloride
NDC: 42806-405 | Form: TABLET, FILM COATED, EXTENDED RELEASE
Manufacturer: EPIC PHARMA, LLC
Category: prescription | Type: HUMAN PRESCRIPTION DRUG LABEL
Date: 20260115

ACTIVE INGREDIENTS: METFORMIN HYDROCHLORIDE 500 mg/1 1
INACTIVE INGREDIENTS: ACETONE; CELLULOSE ACETATE; FERROSOFERRIC OXIDE; HYPROMELLOSE, UNSPECIFIED; MAGNESIUM STEARATE; POLYETHYLENE GLYCOL 400; POLYETHYLENE GLYCOL 8000; POLYSORBATE 80; POVIDONE, UNSPECIFIED; SHELLAC; SODIUM LAURYL SULFATE; TITANIUM DIOXIDE; TRIACETIN

HIGHLIGHTS OF PRESCRIBING INFORMATION

These highlights do not include all the information needed to use metformin hydrochloride extended-release tablets safely and effectively. See full prescribing information for metformin hydrochloride extended-release tablets.
Initial U.S. Approval: 1995

WARNING: LACTIC ACIDOSIS

See full prescribing information for complete boxed warning.

1 INDICATIONS AND USAGE

Metformin hydrochloride extended-release tablets are biguanide indicated as an adjunct to diet and exercise to improve glycemic control in adults with type 2 diabetes mellitus. (1)

2 DOSAGE AND ADMINISTRATION

- Swallow metformin hydrochloride extended-release tablets whole and never crush, cut or chew (2.1)
- Starting dose: 500 mg orally once daily with the evening meal (2.1)
- Increase the dose in increments of 500 mg weekly, up to a maximum of 2,000 mg once daily with the evening meal (2.1)
- Patients receiving metformin hydrochloride (HCl) tablets may be switched to metformin hydrochloride extended-release

Renal Impairment:

- Prior to initiation, assess renal function with estimated glomerular filtration rate (eGFR) (2.2)
- Do not use in patients with eGFR below 30 mL/minute/1.73 m^2 (2.2)
- Initiation is not recommended in patients with eGFR between 30 to 45 mL/minute/1.73 m^2 (2.2)
- Assess risk/benefit of continuing if eGFR falls below 45 mL/minute/1.73 m^2 (2.2)
- Discontinue if eGFR falls below 30 mL/minute/1.73 m^2 (2.2)

Discontinuation for Iodinated Contrast Imaging Procedures:

- Metformin hydrochloride extended-release tablets may need to be discontinued at time of, or prior to, iodinated contrast imaging procedures (2.3)

3 DOSAGE FORMS AND STRENGTHS

Extended-Release Tablets: 500 mg and 1,000 mg (3)

4 CONTRAINDICATIONS

- Severe renal impairment (eGFR below 30 mL/min/1.73 m^2) (4, 5.1)
- Hypersensitivity to metformin (4)
- Acute or chronic metabolic acidosis, including diabetic ketoacidosis, with or without coma. (4)

5 WARNINGS AND PRECAUTIONS

- Lactic Acidosis: See boxed warning. (5.1)
- Vitamin B12 Deficiency: Metformin may lower vitamin B12 levels. Measure hematological parameters annually and vitamin B12 at 2 to 3 year intervals and manage any abnormalities. (5.2)
- Hypoglycemia with Concomitant Use with Insulin and Insulin Secretagogues: Increased risk of hypoglycemia when used in combination with insulin and/or an insulin secretagogue. Lower dose of insulin or insulin secretagogue may be required. (5.3)

6 ADVERSE REACTIONS

Common adverse reactions are diarrhea, nausea/vomiting, abdominal pain, constipation, abdomen distention, dyspepsia/heartburn, flatulence, dizziness, headache, upper respiratory infection, taste disturbance. (6.1)

To report SUSPECTED ADVERSE REACTIONS, contact Epic Pharma, LLC at 1-888-374-2791 or FDA at 1-800-FDA-1088 or www.fda.gov/medwatch.

7 DRUG INTERACTIONS

- Carbonic anhydrase inhibitors may increase risk of lactic acidosis. Consider more frequent monitoring (7)
- Drugs that reduce metformin clearance (such as ranolazine, vandetanib, dolutegravir, and cimetidine) may increase the accumulation of metformin. Consider the benefits and risks of concomitant use (7)
- Alcohol can potentiate the effect of metformin on lactate metabolism. Warn patients against excessive alcohol intake (7)

8 USE IN SPECIFIC POPULATIONS

- Females and Males of Reproductive Potential: Advise premenopausal females of the potential for an unintended pregnancy. (8.3)
- Geriatric Use: Assess renal function more frequently. (8.5)
- Hepatic Impairment: Avoid use in patients with hepatic impairment. (8.7)

FULL PRESCRIBING INFORMATION

WARNING: LACTIC ACIDOSIS

Post-marketing cases of metformin-associated lactic acidosis have resulted in death, hypothermia, hypotension, and resistant bradyarrhythmias. The onset of metformin-associated lactic acidosis is often subtle, accompanied only by nonspecific symptoms such as malaise, myalgias, respiratory distress, somnolence, and abdominal pain. Metformin-associated lactic acidosis was characterized by elevated blood lactate levels (> 5 mmol/Liter), anion gap acidosis (without evidence of ketonuria or ketonemia), an increased lactate/pyruvate ratio; and metformin plasma levels generally >5 mcg/mL [see Warnings and Precautions (5.1)].

Risk factors for metformin-associated lactic acidosis include renal impairment, concomitant use of certain drugs (e.g., carbonic anhydrase inhibitors such as topiramate), age 65 years old or greater, having a radiological study with contrast, surgery and other procedures, hypoxic states (e.g., acute congestive heart failure), excessive alcohol intake, and hepatic impairment.

Steps to reduce the risk of and manage metformin-associated lactic acidosis in these high risk groups are provided [see Dosage and Administration (2.2), Contraindications (4), Warnings and Precautions (5.1)].

If metformin-associated lactic acidosis is suspected, immediately discontinue metformin hydrochloride extended-release tablets and institute general supportive measures in a hospital setting. Prompt hemodialysis is recommended [see Warnings and Precautions (5.1)].

1 INDICATIONS AND USAGE

Metformin hydrochloride extended-release tablets are indicated as an adjunct to diet and exercise to improve glycemic control in adults with type 2 diabetes mellitus.

2 DOSAGE AND ADMINISTRATION

2.1 Adult Dosage and Administration

- Swallow metformin hydrochloride extended-release tablets whole and never crush, cut or chew.
- The recommended starting dose of metformin hydrochloride extended-release tablets is 500 mg orally once daily with the evening meal.
- Increase the dose in increments of 500 mg weekly on the basis of glycemic control and tolerability, up to a maximum of 2,000 mg once daily with the evening meal.
- If glycemic control is not achieved with metformin hydrochloride extended-release tablets 2,000 mg once daily, consider a trial of metformin hydrochloride extended-release tablets 1,000 mg twice daily.
- Patients receiving metformin hydrochloride (HCl) may be switched to metformin hydrochloride extended-release tablets once daily at the same total daily dose, up to 2,000 mg once daily.

2.2 Recommendations for Use in Renal Impairment

- Assess renal function prior to initiation of metformin hydrochloride extended-release tablets and periodically thereafter.
- Metformin hydrochloride extended-release tablets are contraindicated in patients with an estimated glomerular filtration rate (eGFR) below 30 mL/minute/1.73 m^2.
- Initiation of metformin hydrochloride extended-release tablets in patients with an eGFR between 30 to 45 mL/minute/1.73 m^2 is not recommended.
- In patients taking metformin hydrochloride extended-release tablets whose eGFR later falls below 45 mL/min/1.73 m^2, assess the benefit risk of continuing therapy.
- Discontinue metformin hydrochloride extended-release tablets if the patient’s eGFR later falls below 30 mL/minute/1.73 m^2 [see Contraindications (4) and Warnings and Precautions (5.1)].

2.3 Discontinuation for Iodinated Contrast Imaging Procedures

Discontinue metformin hydrochloride extended-release tablets at the time of, or prior to, an iodinated contrast imaging procedure in patients with an eGFR between 30 and 60 mL/min/1.73 m^2; in patients with a history of liver disease, alcoholism, or heart failure; or in patients who will be administered intra-arterial iodinated contrast. Re-evaluate eGFR 48 hours after the imaging procedure; restart metformin hydrochloride extended-release tablets if renal function is stable.

3 DOSAGE FORMS AND STRENGTHS

Metformin hydrochloride extended-release tablets are available as:

- Extended-release tablets: 500 mg white-colored, unscored tablets imprinted with 0019 500 on one side.
- Extended-release tablets: 1,000 mg white-colored, unscored tablets imprinted with 0018 1000 on one side.

4 CONTRAINDICATIONS

Metformin hydrochloride extended-release tablets are contraindicated in patients with:

- Severe renal impairment (eGFR below 30 mL/min/1.73 m^2) [see Warnings and Precautions (5.1)].
- Hypersensitivity to metformin.
- Acute or chronic metabolic acidosis, including diabetic ketoacidosis, with or without coma.

5 WARNINGS AND PRECAUTIONS

5.1 Lactic Acidosis

There have been postmarketing cases of metformin-associated lactic acidosis, including fatal cases. These cases had a subtle onset and were accompanied by nonspecific symptoms such as malaise, myalgias, abdominal pain, respiratory distress, or increased somnolence; however, hypotension and resistant bradyarrhythmias have occurred with severe acidosis. Metforminassociated lactic acidosis was characterized by elevated blood lactate concentrations (> 5 mmol/L), anion gap acidosis (without evidence of ketonuria or ketonemia), and an increased lactate: pyruvate ratio; metformin plasma levels were generally > 5 mcg/mL. Metformin decreases liver uptake of lactate increasing lactate blood levels which may increase the risk of lactic acidosis, especially in patients at risk.

If metformin-associated lactic acidosis is suspected, general supportive measures should be instituted promptly in a hospital setting, along with immediate discontinuation of metformin hydrochloride extended-release tablets. In metformin hydrochloride extended-release tablets treated patients with a diagnosis or strong suspicion of lactic acidosis, prompt hemodialysis is recommended to correct the acidosis and remove accumulated metformin (metformin HCl is dialyzable with a clearance of up to 170 mL/min under good hemodynamic conditions). Hemodialysis has often resulted in reversal of symptoms and recovery.

Educate patients and their families about the symptoms of lactic acidosis and, if these symptoms occur, instruct them to discontinue metformin hydrochloride extended-release tablets and report these symptoms to their healthcare provider.

For each of the known and possible risk factors for metformin-associated lactic acidosis, recommendations to reduce the risk of and manage metformin-associated lactic acidosis are provided below:

- Renal impairment – The postmarketing metformin-associated lactic acidosis cases primarily occurred in patients with significant renal impairment.
The risk of metformin accumulation and metformin-associated lactic acidosis increases with the severity of renal impairment because metformin is substantially excreted by the kidney. Clinical recommendations based upon the patient’s renal function include [see Dosage and Administration (2.2), Clinical Pharmacology (12.3)]:
- Before initiating metformin hydrochloride extended-release tablets, obtain an estimated glomerular filtration rate (eGFR).
- Metformin hydrochloride extended-release tablets are contraindicated in patients with an eGFR less than 30 mL/min/1.73 m^2 [see Contraindications (4)].
- Initiation of metformin hydrochloride extended-release tablets is not recommended in patients with eGFR between 30 to 45 mL/min/1.73 m^2.
- Obtain an eGFR at least annually in all patients taking metformin hydrochloride extended-release tablets. In patients at risk for the development of renal impairment (e.g., the elderly), renal function should be assessed more frequently.
- In patients taking metformin hydrochloride extended-release tablets whose eGFR falls below 45 mL/min/1.73 m^2, assess the benefit and risk of continuing therapy.
- Drug interactions – The concomitant use of metformin hydrochloride extended-release tablets with specific drugs may increase the risk of metformin-associated lactic acidosis: those that impair renal function, result in significant hemodynamic change, interfere with acid-base balance, or increase metformin accumulation [see Drug Interactions (7)]. Consider more frequent monitoring of patients.
- Age 65 or greater – The risk of metformin-associated lactic acidosis increases with the patient’s age because elderly patients have a greater likelihood of having hepatic, renal, or cardiac impairment than younger patients. Assess renal function more frequently in elderly patients.
- Radiologic studies with contrast – Administration of intravascular iodinated contrast agents in metformin-treated patients has led to an acute decrease in renal function and the occurrence of lactic acidosis. Stop metformin hydrochloride extended-release tablets at the time of, or prior to, an iodinated contrast imaging procedure in patients with an eGFR between 30 and 60 mL/min/1.73 m2; in patients with a history of hepatic impairment, alcoholism or heart failure; or in patients who will be administered intra-arterial iodinated contrast. Re-evaluate eGFR 48 hours after the imaging procedure, and restart metformin hydrochloride extended-release tablets if renal function is stable.
- Surgery and other procedures – Withholding of food and fluids during surgical or other procedures may increase the risk for volume depletion, hypotension, and renal impairment. Metformin hydrochloride extended-release tablets should be temporarily discontinued while patients have restricted food and fluid intake.
- Hypoxic states – Several of the postmarketing cases of metformin-associated lactic acidosis occurred in the setting of acute congestive heart failure (particularly when accompanied by hypoperfusion and hypoxemia). Cardiovascular collapse (shock), acute myocardial infarction, sepsis, and other conditions associated with hypoxemia have been associated with lactic acidosis and may cause prerenal azotemia. When such an event occurs, discontinue metformin hydrochloride extended-release tablets.
- Excessive alcohol intake – Alcohol potentiates the effect of metformin on lactate metabolism. Patients should be warned against excessive alcohol intake while receiving metformin hydrochloride extended-release tablets.
- Hepatic impairment – Patients with hepatic impairment have developed cases of metformin-associated lactic acidosis. This may be due to impaired lactate clearance resulting in higher lactate blood levels. Therefore, avoid use of metformin hydrochloride extended-release tablets in patients with clinical or laboratory evidence of hepatic disease.

5.2 Vitamin B12 Deficiency

In clinical trials of 29-week duration with metformin HCl tablets, a decrease to subnormal levels of previously normal serum vitamin B12 levels was observed in approximately 7% of patients. Such decrease, possibly due to interference with B12 absorption from the B12-intrinsic factor complex, may be associated with anemia but appears to be rapidly reversible with discontinuation of metformin or vitamin B12 supplementation. Certain individuals (those with inadequate vitamin B12 or calcium intake or absorption) appear to be predisposed to developing subnormal vitamin B12 levels. Measure hematologic parameters on an annual basis and vitamin B12 at 2 to 3 year intervals in patients on metformin hydrochloride extended-release tablets and manage any abnormalities [see Adverse Reactions (6.1)].

5.3 Hypoglycemia with Concomitant Use with Insulin and Insulin Secretagogues

Insulin and insulin secretagogues (e.g., sulfonylurea) are known to cause hypoglycemia. Metformin hydrochloride extended-release tablets may increase the risk of hypoglycemia when combined with insulin and/or an insulin secretagogue. Therefore, a lower dose of insulin or insulin secretagogue may be required to minimize the risk of hypoglycemia when used in combination with metformin hydrochloride extended-release tablets [see Drug Interactions (7)].

5.4 Macrovascular Outcomes

There have been no clinical studies establishing conclusive evidence of macrovascular risk reduction with metformin hydrochloride extended-release tablets.

6 ADVERSE REACTIONS

The following adverse reactions are also discussed elsewhere in the labeling:

- Lactic Acidosis [see Error! Hyperlink reference not valid. and Warnings and Precautions (5.1)]
- Vitamin B12 Deficiency [see Warnings and Precautions (5.2)]
- Hypoglycemia [see Warnings and Precautions (5.3)]

6.1 Clinical Studies Experience

Because clinical trials are conducted under widely varying conditions, adverse reaction rates observed in the clinical trials of a drug cannot be directly compared to rates in the clinical trials of another drug and may not reflect the rates observed in practice.

In placebo-controlled trials, 781 patients were administered metformin HCl extended-release tablets. Adverse reactions reported in greater than 5% of the patients treated with metformin HCl extended-release tablets and that were more common than in placebo-treated patients are listed in Table 1.

Table 1: Adverse Reactions from Clinical Trials of Metformin HCl Extended-Release Tablets Occurring >5% and More Common than Placebo in Patients with Type 2 Diabetes Mellitus

Adverse Reaction | Metformin HCl Extended-Release Tablets; (n=781) | Placebo; (n=195)
Diarrhea | 10% | 3%
Nausea/Vomiting | 7% | 2%

Diarrhea led to the discontinuation of metformin HCl extended-release tablets in 0.6% of patients. Additionally, the following adverse reactions were reported in 1.0% to 5.0% of patients treated with metformin HCl extended-release tablets and were more commonly reported than in placebo-treated patients: abdominal pain, constipation, abdomen distention, dyspepsia/ heartburn, flatulence, dizziness, headache, upper respiratory infection, taste disturbance.

Laboratory Tests

Vitamin B12 Concentrations

In clinical trials of 29-week duration with metformin HCl tablets, a decrease to subnormal levels of previously normal serum vitamin B12 levels was observed in approximately 7% of patients.

6.2 Postmarketing Experience

The following adverse reactions have been identified during post approval use of metformin. Because these reactions are reported voluntarily from a population of uncertain size, it is not always possible to reliably estimate their frequency or establish a causal relationship to drug exposure.

Cholestatic, hepatocellular, and mixed hepatocellular liver injury have been reported with postmarketing use of metformin.

7 DRUG INTERACTIONS

Table 2 presents clinically significant drug interactions with metformin hydrochloride extended-release tablets.

Table 2: Clinically Significant Drug Interactions with Metformin Hydrochloride Extended-Release Tablets

Carbonic Anhydrase Inhibitors
Clinical Impact: | Carbonic anhydrase inhibitors frequently cause a decrease in serum bicarbonate and induce non-anion gap, hyperchloremic metabolic acidosis. Concomitant use of these drugs with metformin hydrochloride extended-release tablets may increase the risk for lactic acidosis.
Intervention: | Consider more frequent monitoring of these patients.
Examples: | Topiramate, zonisamide, acetazolamide or dichlorphenamide.
Drugs that Reduce Metformin Hydrochloride Extended-Release Tablets Clearance
Clinical Impact: | Concomitant use of drugs that interfere with common renal tubular transport systems involved in the renal elimination of metformin (e.g., organic cationic transporter-2 [OCT2] / multidrug and toxin extrusion [MATE] inhibitors) could increase systemic exposure to metformin and may increase the risk for lactic acidosis [see Clinical Pharmacology (12.3)].
Intervention: | Consider the benefits and risks of concomitant use with metformin hydrochloride extended-release tablets.
Examples: | Ranolazine, vandetanib, dolutegravir, and cimetidine.
Alcohol
Clinical Impact: | Alcohol is known to potentiate the effect of metformin on lactate metabolism.
Intervention: | Warn patients against excessive alcohol intake while receiving metformin hydrochloride extended-release tablets.
Insulin Secretagogues or Insulin
Clinical Impact: | Coadministration of metformin hydrochloride extended-release tablets with an insulin secretagogue (e.g., sulfonylurea) or insulin may increase the risk of hypoglycemia.
Intervention: | Patients receiving an insulin secretagogue or insulin may require lower doses of the insulin secretagogue or insulin.
Drugs Affecting Glycemic Control
Clinical Impact: | Certain drugs tend to produce hyperglycemia and may lead to loss of glycemic control.
Intervention: | When such drugs are administered to a patient receiving metformin hydrochloride extended-release tablets, observe the patient closely for loss of blood glucose control. When such drugs are withdrawn from a patient receiving metformin hydrochloride extended-release tablets, observe the patient closely for hypoglycemia.
Examples: | Thiazides and other diuretics, corticosteroids, phenothiazines, thyroid products, estrogens, oral contraceptives, phenytoin, nicotinic acid, sympathomimetics, calcium channel blockers, and isoniazid.

8 USE IN SPECIFIC POPULATIONS

8.1 Pregnancy

Risk Summary

Limited data with metformin hydrochloride extended-release tablets in pregnant women are not sufficient to determine a drug-associated risk for major birth defects or miscarriage. Published studies with metformin use during pregnancy have not reported a clear association with metformin and major birth defect or miscarriage risk [see Data]. There are risks to the mother and fetus associated with poorly controlled diabetes mellitus in pregnancy [see Clinical Considerations].

No adverse developmental effects were observed when metformin was administered to pregnant Sprague Dawley rats and rabbits during the period of organogenesis at doses up to 2- and 5-times, respectively, a 2550 mg clinical dose, based on body surface area [see Data].

The estimated background risk of major birth defects is 6 to 10% in women with pre-gestational diabetes mellitus with an HbA1c >7 and has been reported to be as high as 20 to 25% in women with a HbA1c >10. The estimated background risk of miscarriage for the indicated population is unknown. In the U.S. general population, the estimated background risk of major birth defects and miscarriage in clinically recognized pregnancies is 2 to 4% and 15 to 20%, respectively.

Clinical Considerations

Disease-associated maternal and/or embryo/fetal risk

Poorly-controlled diabetes mellitus in pregnancy increases the maternal risk for diabetic ketoacidosis, pre-eclampsia, spontaneous abortions, preterm delivery, stillbirth and delivery complications. Poorly controlled diabetes mellitus increases the fetal risk for major birth defects, stillbirth, and macrosomia related morbidity.

Data

Human Data

Published data from post-marketing studies have not reported a clear association with metformin and major birth defects, miscarriage, or adverse maternal or fetal outcomes when metformin was used during pregnancy. However, these studies cannot definitely establish the absence of any metformin-associated risk because of methodological limitations, including small sample size and inconsistent comparator groups.

Animal Data

Metformin HCl did not adversely affect development outcomes when administered to pregnant rats and rabbits at doses up to 600 mg/kg/day. This represents an exposure of about 2 and 5 times a 2550 mg clinical dose based on body surface area comparisons for rats and rabbits, respectively. Determination of fetal concentrations demonstrated a partial placental barrier to metformin.

8.2 Lactation

Risk Summary

Limited published studies report that metformin is present in human milk [see Data]. However, there is insufficient information to determine the effects of metformin on the breastfed infant and no available information on the effects of metformin on milk production. Therefore, the developmental and health benefits of breastfeeding should be considered along with the mother’s clinical need for metformin hydrochloride extended-release tablets and any potential adverse effects on the breastfed child from metformin hydrochloride extended-release tablets or from the underlying maternal condition.

Data

Published clinical lactation studies report that metformin is present in human milk which resulted in infant doses approximately 0.11% to 1% of the maternal weight-adjusted dosage and a milk/ plasma ratio ranging between 0.13 and 1. However, the studies were not designed to definitely establish the risk of use of metformin during lactation because of small sample size and limited adverse event data collected in infants.

8.3 Females and Males of Reproductive Potential

Discuss the potential for unintended pregnancy with premenopausal women as therapy with metformin hydrochloride extended-release tablets may result in ovulation in some anovulatory women.

8.4 Pediatric Use

Safety and effectiveness of metformin hydrochloride extended-release tablets in pediatric patients have not been established.

8.5 Geriatric Use

Controlled clinical studies of metformin hydrochloride extended-release tablets did not include sufficient numbers of elderly patients to determine whether they respond differently from younger patients. In general, dose selection for an elderly patient should be cautious, usually starting at the low end of the dosing range, reflecting the greater frequency of decreased hepatic, renal, or cardiac function, and of concomitant disease or other drug therapy and the higher risk of lactic acidosis. Assess renal function more frequently in elderly patients [see Warnings and Precautions (5.1)].

8.6 Renal Impairment

Metformin is substantially excreted by the kidney, and the risk of metformin accumulation and lactic acidosis increases with the degree of renal impairment. Metformin hydrochloride extended-release tablets are contraindicated in severe renal impairment, patients with an estimated glomerular filtration rate (eGFR) below 30 mL/min/1.73 m^2 [see Dosage and Administration (2.2), Contraindications (4), Warnings and Precautions (5.1), and Clinical Pharmacology (12.3)].

8.7 Hepatic Impairment

Use of metformin in patients with hepatic impairment has been associated with some cases of lactic acidosis.

Metformin hydrochloride extended-release tablets are not recommended in patients with hepatic impairment [see Warnings and Precautions (5.1)].

10 OVERDOSAGE

Overdose of metformin HCl has occurred, including ingestion of amounts greater than 50 grams. Hypoglycemia was reported in approximately 10% of cases, but no causal association with metformin has been established. Lactic acidosis has been reported in approximately 32% of metformin overdose cases [see Warnings and Precautions (5.1)]. Metformin is dialyzable with a clearance of up to 170 mL/min under good hemodynamic conditions. Therefore, hemodialysis may be useful for removal of accumulated drug from patients in whom metformin overdosage is suspected.

11 DESCRIPTION

Metformin hydrochloride extended-release tablets contain the biguanidine antihyperglycemic agent, metformin, in the form of monohydrochloride salt. The chemical name of metformin HCl is N, N-dimethylimidodicarbonimidic diamide hydrochloride with a molecular formula of C4H11N5•HCl and a molecular weight of 165.63. Its structural formula is:

Metformin HCl is a white or almost white crystals powder that is freely soluble in water and is practically insoluble in acetone, ether, and chloroform. The pKa of metformin is 12.4. The pH of a 1% aqueous solution of metformin HCl is 6.68.

Metformin hydrochloride extended-release tablets deliver 500 mg or 1,000 mg of metformin HCl, which is equivalent to 389.93 mg or 779.86 mg metformin, respectively. In addition to the active ingredient metformin HCl, each tablet contains the following inactive ingredients: Povidone, Sodium Lauryl Sulfate, Magnesium Stearate, Cellulose Acetate, Polyethylene Glycol (PEG 400, PEG 8000), Triacetin, Hypromellose, Titanium Dioxide, Polysorbate 80, Ferrosoferric Oxide, Shellac.

Metformin Meets USP Dissolution Test 5.

12 CLINICAL PHARMACOLOGY

12.1 Mechanism of Action

Metformin is an antihyperglycemic agent which improves glucose tolerance in patients with type 2 diabetes mellitus, lowering both basal and postprandial plasma glucose. Metformin decreases hepatic glucose production, decreases intestinal absorption of glucose, and improves insulin sensitivity by increasing peripheral glucose uptake and utilization. With metformin therapy, insulin secretion remains unchanged while fasting insulin levels and day-long plasma insulin response may decrease.

12.3 Pharmacokinetics

Absorption

In a multiple-dose crossover study, 23 patients with type 2 diabetes mellitus were administered either metformin hydrochloride extended-release tablets 2,000 mg once a day (after dinner) or metformin HCl tablets 1,000 mg twice a day (after breakfast and after dinner). After 4 weeks of treatment, steady-state pharmacokinetic parameters, area under the concentration-time curve (AUC), time to peak plasma concentration (Tmax), and maximum concentration (Cmax) were evaluated. The appearance of metformin in plasma from metformin hydrochloride extended-release tablets is slower and more prolonged compared to metformin HCl tablets. Results are presented in Table 3.

Table 3
Metformin Hydrochloride Extended-Release Tablets vs. Metformin HCl Tablets
Steady-State Pharmacokinetic Parameters at 4 Weeks
Pharmacokinetic; Parameters; (mean ± SD) | Metformin Hydrochloride Extended-; Release Tablets 2,000 mg; (administered q.d. after dinner) | Metformin HCl tablets*; 2,000 mg; (1,000 mg b.i.d.)
AUC0-24hr (ng•hr/mL) | 26,811 ± 7055 | 27,371 ± 5,781
Tmax (hr) | 6 (3-10) | 3 (1-8)
Cmax (ng/mL) | 2849 ± 797 | 1820 ± 370

*Immediate-release metformin HCl tablets

In four single-dose studies and one multiple-dose study, the bioavailability of metformin hydrochloride extended-release tablets 2,000 mg given once daily, in the evening, under fed conditions [as measured by AUC] was similar to the same total daily dose administered as metformin HCl tablets 1,000 mg given twice daily. The geometric mean ratios (metformin hydrochloride extended-release tablets / metformin HCL tablets) of AUC0-24hr, AUC0-72hr, and AUC0-inf for these five studies ranged from 0.96 to 1.08.

In a single-dose, four-period replicate crossover design study, comparing two 500 mg metformin hydrochloride extended-release tablets to one 1,000 mg metformin hydrochloride extended-release tablet administered in the evening with food to 29 healthy male subjects, two 500 mg metformin hydrochloride extended-release tablets were found to be equivalent to one 1,000 mg metformin hydrochloride extended-release tablet.

In a study carried out with metformin hydrochloride extended-release tablets, there was a dose-associated increase in metformin exposure over 24 hours following oral administration of 1,000, 1,500, 2,000, and 2,500 mg.

In three studies with metformin hydrochloride extended-release tablets using different treatment regimens (2,000 mg after dinner; 1,000 mg after breakfast and after dinner; and 2,500 mg after dinner), the pharmacokinetics of metformin as measured by AUC appeared linear following multiple-dose administration.

Effect of food: The extent of metformin absorption (as measured by AUC) from metformin hydrochloride extended-release tablets increased by approximately 60% when given with food. When metformin hydrochloride extended-release tablets were administered with food, Cmax was increased by approximately 30% and Tmax was more prolonged compared with the fasting state (6.1 versus 4.0 hours).

Distribution

The apparent volume of distribution (V/F) of metformin following single oral doses of metformin HCl tablets 850 mg averaged 654 ± 358 L. Metformin is negligibly bound to plasma proteins. Metformin partitions into erythrocytes, most likely as a function of time.

Metabolism

Intravenous single-dose studies in normal subjects demonstrate that metformin is excreted unchanged in the urine and does not undergo hepatic metabolism (no metabolites have been identified in humans) nor biliary excretion.

Elimination

Renal clearance (see Table 4) is approximately 3.5 times greater than creatinine clearance, which indicates that tubular secretion is the major route of metformin elimination. Following oral administration, approximately 90% of the absorbed drug is eliminated via the renal route within the first 24 hours, with a plasma elimination half-life of approximately 6.2 hours. In blood, the elimination half-life is approximately 17.6 hours, suggesting that the erythrocyte mass may be a compartment of distribution.

Specific Populations

Renal Impairment

In patients with decreased renal function the plasma and blood half-life of metformin is prolonged and the renal clearance is decreased (see Table 4) [see Dosage and Administration (2.2), Contraindications (4), and Warnings and Precautions (5.1) and Use in Specific Populations (8.6)].

Hepatic Impairment

No pharmacokinetic studies of metformin have been conducted in patients with hepatic impairment [see Warnings and Precautions (5.1) and Use in Specific Populations (8.7)].

Geriatrics

Limited data from controlled pharmacokinetic studies of metformin HCl tablets in healthy elderly subjects suggest that total plasma clearance of metformin is decreased, the half-life is prolonged, and Cmax is increased, compared to healthy young subjects. It appears that the change in metformin pharmacokinetics with aging is primarily accounted for by a change in renal function (see Table 4) [seeWarnings and Precautions (5.1) and Use in Specific Populations (8.5)].

Table 4: Select Mean (±S.D.) Metformin Pharmacokinetic Parameters Following Single or Multiple Oral Doses of Metformin HCl Tablets

Subject Groups: Metformin HCl dosea; (number of subjects) | Cmaxb; (mcg/mL) | Tmaxc; (hrs) | Renal Clearance; (mL/min)
Healthy, nondiabetic adults:
500 mg single dose (24); 850 mg single dose (74)d; 850 mg three times daily for 19 dosese (9) | 1.03 (±0.33); 1.60 (±0.38); 2.01 (±0.42) | 2.75 (±0.81); 2.64 (±0.82); 1.79 (±0.94) | 600 (±132); 552 (±139); 642 (±173)
Adults with type 2 diabetes mellitus:
850 mg single dose (23); 850 mg three times daily for 19 dosese (9) | 1.48 (±0.5); 1.90 (±0.62) | 3.32 (±1.08); 2.01 (±1.22) | 491 (±138); 550 (±160)
Elderlyf, healthy nondiabetic adults:
850 mg single dose (12) | 2.45 (±0.70) | 2.71 (±1.05) | 412 (±98)
Renal-impaired adults:
850 mg single dose; Mild (CLcrg 61 to 90 mL/min) (5) Moderate (CLcr 31 to 60 mL/min) (4) Severe (CLcr 10 to 30 mL/min) (6) | 1.86 (±0.52); 4.12 (±1.83); 3.93 (±0.92) | 3.20 (±0.45); 3.75 (±0.50); 4.01 (±1.10) | 384 (±122); 108 (±57); 130 (±90)

a All doses given fasting except the first 18 doses of the multiple dose studies

b Peak plasma concentration

c Time to peak plasma concentration

d Combined results (average means) of five studies: mean age 32 years (range 23 to 59 years)

e Kinetic study done following dose 19, given fasting

f Elderly subjects, mean age 71 years (range 65 to 81 years)

g CLcr = creatinine clearance normalized to body surface area of 1.73 m^2

Pediatrics

There are no available pharmacokinetic data with metformin hydrochloride extended-release tablets in pediatric patients.

Gender

Metformin pharmacokinetic parameters did not differ significantly between normal subjects and patients with type 2 diabetes mellitus when analyzed according to gender (males=19, females=16).

Race

No studies of metformin pharmacokinetic parameters according to race have been performed.

Drug Interactions

In Vivo Assessment of Drug Interactions

Table 5: Effect of Coadministered Drug on Plasma Metformin Systemic Exposure

Coadministered; Drug | Dose of; Coadministered; Drug* | Dose of; Metformin; HCl* | Geometric Mean Ratio; (ratio with/without coadministered drug); No Effect = 1.00
Coadministered; Drug | Dose of; Coadministered; Drug* | Dose of; Metformin; HCl* |  | AUC† | Cmax
No dosing adjustments required for the following:
Glyburide | 5 mg | 850 mg | metformin | 0.91‡ | 0.93‡
Furosemide | 40 mg | 850 mg | metformin | 1.09‡ | 1.22‡
Nifedipine | 10 mg | 850 mg | metformin | 1.16 | 1.21
Propranolol | 40 mg | 850 mg | metformin | 0.90 | 0.94
Ibuprofen | 400 mg | 850 mg | metformin | 1.05‡ | 1.07‡
Cationic drugs eliminated by renal tubular secretion may reduce metformin elimination
[see Warnings and Precautions (5.1) and Drug Interactions (7).]
Cimetidine | 400 mg | 850 mg | metformin | 1.40 | 1.61
Carbonic anhydrase inhibitors may cause metabolic acidosis
[see Warnings and Precautions (5.1) and Drug Interactions (7).]
Topiramate | 100 mg§ | 500 mg§ | metformin | 1.25§ | 1.17

* All metformin HCl and coadministered drugs were given as single doses

† AUC = AUCinf

‡ Ratio of arithmetic means

§ At steady state with topiramate 100 mg every 12 hours and metformin 500 mg every 12 hours;

AUC = AUC0-12h

Table 6: Effect of Metformin on Coadministered Drug Systemic Exposure

Coadministered; Drug | Dose of; Coadministered; Drug* | Dose of; Metformin; HCl* | Geometric Mean Ratio; (ratio with/without coadministered drug); No Effect = 1.00
Coadministered; Drug | Dose of; Coadministered; Drug* | Dose of; Metformin; HCl* |  | AUC† | Cmax
No dosing adjustments required for the following:
Glyburide | 5 mg | 850 mg | Glyburide | 0.78‡ | 0.63‡
Furosemide | 40 mg | 850 mg | Furosemide | 0.87‡ | 0.69‡
Nifedipine | 10 mg | 850 mg | Nifedipine | 1.10§ | 1.08
Propranolol | 40 mg | 850 mg | Propranolol | 1.01§ | 1.02
Ibuprofen | 400 mg | 850 mg | Ibuprofen | 0.97¶ | 1.01¶
Cimetidine | 400 mg | 850 mg | Cimetidine | 0.95§ | 1.01

* All metformin HCl and coadministered drugs were given as single doses

† AUC = AUCinf unless otherwise noted

‡ Ratio of arithmetic means, p-value of difference <0.05

§ AUC0-24 hr reported

¶ Ratio of arithmetic means

13 NONCLINICAL TOXICOLOGY

13.1 Carcinogenesis, Mutagenesis, Impairment of Fertility

Long-term carcinogenicity studies have been performed in rats (dosing duration of 104 weeks) and mice (dosing duration of 91 weeks) at doses up to and including 900 mg/kg/day and 1,500 mg/kg/day, respectively. These doses are both approximately 3 times the maximum recommended human daily dose of 2550 mg based on body surface area comparisons. No evidence of carcinogenicity with metformin was found in either male or female mice. Similarly, there was no tumorigenic potential observed with metformin in male rats. There was, however, an increased incidence of benign stromal uterine polyps in female rats treated with 900 mg/kg/day.

There was no evidence of a mutagenic potential of metformin in the following in vitro tests: Ames test (S. typhimurium), gene mutation test (mouse lymphoma cells), or chromosomal aberrations test (human lymphocytes). Results in the in vivo mouse micronucleus test were also negative.

Fertility of male or female rats was unaffected by metformin when administered at doses as high as 600 mg/kg/day, which is approximately 2 times the maximum recommended human daily dose of 2550 mg based on body surface area comparisons.

14 CLINICAL STUDIES

A 24-week, double-blind, placebo-controlled study of metformin HCl extended-release tablets, taken once daily with the evening meal, was conducted in patients with type 2 diabetes mellitus who had failed to achieve glycemic control with diet and exercise. Patients entering the study had a mean baseline HbA1c of 8.0% and a mean baseline FPG of 176 mg/dL. The treatment dose was increased to 1,500 mg once daily if at Week 12 HbA1c was ‑7.0% but <8.0% (patients with HbA1c‑8.0% were discontinued from the study). At the final visit (24-week), mean HbA1c had increased 0.2% from baseline in placebo patients and decreased 0.6% with metformin HCl extended-release tablets.

A 16-week, double-blind, placebo-controlled, dose-response study of metformin HCl extended-release tablets, taken once daily with the evening meal or twice daily with meals, was conducted in patients with type 2 diabetes mellitus who had failed to achieve glycemic control with diet and exercise. The results are shown in Table 7.

Table 7: Mean Changes from Baseline* in HbA1c and Fasting Plasma Glucose at Week 16 Comparing Metformin HCl Extended-Release Tablets vs Placebo in Patients with Type 2 Diabetes Mellitus

 | Metformin HCl Extended-Release Tablets |  |  |  |  | Placebo
 | 500 mg; Once; Daily | 1,000 mg; Once; Daily | 1,500 mg; Once; Daily | 2,000 mg; Once; Daily | 1,000 mg; Twice; Daily | Placebo
Hemoglobin A1c (%); Baseline Change at FINAL VISIT p-valuea | (n=115); 8.2; –0.4; <0.001 | (n=115); 8.4; –0.6; <0.001 | (n=111); 8.3; –0.9; <0.001 | (n=125); 8.4; –0.8; <0.001 | (n=112); 8.4; –1.1; <0.001 | (n=111); 8.4; 0.1; –
FPG (mg/dL); Baseline Change at FINAL VISIT p-valuea | (n=126); 182.7; –15.2; <0.001 | (n=118); 183.7; –19.3; <0.001 | (n=120); 178.9; –28.5; <0.001 | (n=132); 181.0; –29.9; <0.001 | (n=122); 181.6; –33.6; <0.001 | (n=113); 179.6; 7.6; –

a All comparisons versus Placebo

Mean baseline body weight was 193 lbs, 192 lbs, 188 lbs, 196 lbs, 193 lbs and 194 lbs in the metformin HCl extended-release tablets 500 mg, 1,000 mg, 1,500 mg, and 2,000 mg once daily, 1,000 mg twice daily and placebo arms, respectively. Mean change in body weight from baseline to week 16 was -1.3 lbs, -1.3 lbs, -0.7 lbs, -1.5 lbs, -2.2 lbs and -1.8 lbs, respectively.

A 24-week, double-blind, randomized study of metformin HCl extended-release tablets, taken once daily with the evening meal, and metformin HCl tablets, taken twice daily (with breakfast and evening meal), was conducted in patients with type 2 diabetes mellitus who had been treated with metformin HCl tablets 500 mg twice daily for at least 8 weeks prior to study entry. The results are shown in Table 8.

Table 8: Mean Changes from Baseline* in HbA1c and Fasting Plasma Glucose at Week 24 Comparing Metformin HCl Extended-Release vs Metformin HCl in Patients with Type 2 Diabetes Mellitus

 | Metformin HCl; 500 mg; Twice Daily | Metformin HCl Extended-Release
 | Metformin HCl; 500 mg; Twice Daily | 1,000 mg; Once Daily | 1,500 mg; Once Daily
Hemoglobin A1c (%); Baseline Change at FINAL VISIT (95% CI) | (n=67); 7.06; 0.14a; (–0.04, 0.31) | (n=72); 6.99; 0.27; (0.11, 0.43) | (n=66); 7.02; 0.13; (–0.02, 0.28)
FPG (mg/dL); Baseline Change at FINAL VISIT (95% CI) | (n=69); 127.2; 14.0; (7.0, 21.0) | (n=72); 131.0; 11.5; (4.4, 18.6) | (n=70); 131.4; 7.6; (1.0, 14.2)

†a n=68

Mean baseline body weight was 210 lbs, 203 lbs and 193 lbs in the metformin HCl tablets 500 mg twice daily, and metformin HCl extended-release tablets 1,000 mg and 1,500 mg once daily arms, respectively. Mean change in body weight from baseline to week 24 was 0.9 lbs, 1.1 lbs and 0.9 lbs, respectively.

16 HOW SUPPLIED/STORAGE AND HANDLING

16.1 How Supplied

Metformin hydrochloride extended-release tablets are supplied as:

500 mg | Bottles of 60 | NDC 42806-405-60 | white-colored, unscored biconvex-shaped, film-coated extended-release tablets imprinted with 0019 500 on one side.
1,000 mg | Bottles of 60 | NDC 42806-406-60 | white-colored, unscored biconvex-shaped, film-coated extended-release tablets imprinted with 0018 1000 on one side.

16.2 Storage

Store at 20° to 25°C (68° to 77°F) [See USP Controlled Room Temperature] excursions permitted to 15° to 30°C (59° to 86°F). Avoid excessive heat and humidity.

Keep tightly closed (protect from moisture). Protect from light.

17 PATIENT COUNSELING INFORMATION

Advise the patient to read the FDA-approved patient labeling (Patient Information).

Lactic Acidosis:

Explain the risks of lactic acidosis, its symptoms, and conditions that predispose to its development. Advise patients to discontinue metformin hydrochloride extended-release tablets immediately and to promptly notify their healthcare provider if unexplained hyperventilation, myalgias, malaise, unusual somnolence or other nonspecific symptoms occur. Counsel patients against excessive alcohol intake and inform patients about importance of regular testing of renal function while receiving metformin hydrochloride extended-release tablets. Instruct patients to inform their doctor that they are taking metformin hydrochloride extended-release tablets prior to any surgical or radiological procedure, as temporary discontinuation may be required [see Warnings and Precautions (5.1)].

Hypoglycemia:

Inform patients that hypoglycemia may occur when metformin hydrochloride extended-release tablets are coadministered with oral sulfonylureas and insulin. Explain to patients receiving concomitant therapy the risks of hypoglycemia, its symptoms and treatment, and conditions that predispose to its development [see Warnings and Precautions (5.3)].

Vitamin B12 Deficiency:

Inform patients about importance of regular hematological parameters while receiving metformin hydrochloride extended-release tablets [see Warnings and Precautions (5.2)].

Females of Reproductive Age:

Inform females that treatment with metformin hydrochloride extended-release tablets may result in ovulation in some premenopausal anovulatory women which may lead to unintended pregnancy [see Use in Specific Populations (8.3)].

Administration Information:

Inform patients that metformin hydrochloride extended-release tablets must be swallowed whole and not crushed, cut, or chewed, and that the inactive ingredients may occasionally be eliminated in the feces as a soft mass that may resemble the original tablet.

Manufactured by:

Qingdao BAHEAL Pharmaceutical Co., Ltd.

NO.268 Yingcheng Road, Jimo, Qingdao PR China

Distributed by:

Epic Pharma LLC

Laurelton, NY 11413

Rev. 02/19

Patient Medication Information

PATIENT INFORMATION

Metformin hydrochloride

extended-release tablets

What is the most important information I should know about metformin hydrochloride extended-release tablets?

Metformin hydrochloride extended-release tablets can cause serious side effects including:

Lactic Acidosis. Metformin hydrochloride, the medicine in metformin hydrochloride extended-release tablets, can cause a rare, but serious side effect called lactic acidosis (a build-up of lactic acid in the blood) that can cause death. Lactic acidosis is a medical emergency and must be treated in a hospital.

Stop taking metformin hydrochloride extended-release tablets and call your healthcare provider right away if you get any of the following symptoms of lactic acidosis:

- feel very weak and tired
- have unusual sleepiness or sleep longer than usual
- have unusual (not normal) muscle pain
- feel cold, especially in your arms and legs
- have trouble breathing
- feel dizzy or lightheaded
- have unexplained stomach or intestinal problems with nausea and vomiting, or diarrhea
- have a slow or irregular heartbeat

You have a higher chance of getting lactic acidosis if you:

- have severe kidney problems. See “Do not take metformin hydrochloride extended-release tablets if you:”
- have liver problems.
- have congestive heart failure that requires treatment with medicines.
- drink a lot of alcohol (very often or short-term “binge” drinking).
- get dehydrated (lose a large amount of body fluids). This can happen if you are sick with a fever, vomiting, or diarrhea. Dehydration can also happen when you sweat a lot with activity or exercise and do not drink enough fluids.
- have certain x-ray tests with injectable dyes or contrast agents.
- have surgery.
- have a heart attack, severe infection, or stroke.
- are 65 years of age or older.

Tell your healthcare provider if you have any of the problems in the list above.

Tell your healthcare provider that you are taking metformin hydrochloride extended-release tablets before you have surgery or x-ray tests. Your healthcare provider may need to stop metformin hydrochloride extended-release tablets for a while if you have surgery or certain x-ray tests.

Metformin hydrochloride extended-release tablets can have other serious side effects. See “What are the possible side effects of metformin hydrochloride extended-release tablets?”

What are metformin hydrochloride extended-release tablets?

- Metformin hydrochloride extended-release tablets are prescription medicine that contain metformin hydrochloride. Metformin hydrochloride extended-release tablets are used with diet and exercise to help control high blood sugar (hyperglycemia) in adults with type 2 diabetes.
- It is not known if metformin hydrochloride extended-release tablets are safe and effective in children under 18 years of age.

Do not take metformin hydrochloride extended-release tablets if you:

- have severe kidney problems
- are allergic to metformin HCl or any of the ingredients in metformin hydrochloride extended-release tablets. See the end of this Patient Information leaflet for a complete list of ingredients in metformin hydrochloride extended-release tablets.
- have a condition called metabolic acidosis including diabetic ketoacidosis (high levels of certain acids called “ketones” in your blood or urine).

Before taking metformin hydrochloride extended-release tablets, tell your healthcare provider about all your medical conditions, including if you:

- have a history or risk for diabetic ketoacidosis. See “Do not take metformin hydrochloride extended-release tablets if you:”
- have kidney problems.
- have liver problems.
- have heart problems, including congestive heart failure.
- are 65 years of age or older.
- drink alcohol very often or drink a lot of alcohol in short-term “binge” drinking.
- are taking insulin or a sulfonylurea medicine.
- are pregnant or plan to become pregnant. It is not known if metformin hydrochloride extended-release tablets will harm your unborn baby. If you are pregnant, talk with your healthcare provider about the best way to control your blood sugar while you are pregnant.
- are a woman who has not gone through menopause (premenopausal) who does not have periods regularly or at all. Metformin hydrochloride extended-release tablets can cause the release of an egg from an ovary in a woman (ovulation). This can increase your chance of getting pregnant.
- are breastfeeding or plan to breastfeed. Metformin hydrochloride extended-release tablets can pass into your breast milk. Talk with your healthcare provider about the best way to feed your baby while you take metformin hydrochloride extended-release tablets.

Tell your healthcare provider about all the medicines you take, including prescription and over-the-counter medicines, vitamins, and herbal supplements. Know the medicines you take. Keep a list of them to show your healthcare provider and pharmacist when you get a new medicine.

Metformin hydrochloride extended-release tablets may affect the way other medicines work, and other medicines may affect how metformin hydrochloride extended-release tablets work.

How should I take metformin hydrochloride extended-release tablets?

- Take metformin hydrochloride extended-release tablets exactly as your healthcare provider tells you.
- Metformin hydrochloride extended-release tablets should be taken with your evening meals to help decrease an upset stomach.
- Swallow metformin hydrochloride extended-release tablets whole. Do not crush, cut, or chew the tablets.
- You may sometimes pass a soft mass in your stools (bowel movement) that looks like metformin hydrochloride extended-release tablets. This is not harmful and will not affect the way metformin hydrochloride extended-release tablets works.
- When your body is under some types of stress, such as fever, trauma (such as a car accident), infection, or surgery, the amount of diabetes medicine that you need may change. Tell your healthcare provider right away if you have any of these problems.
- Your healthcare provider should do blood tests to check how well your kidneys are working before and during your treatment with metformin hydrochloride extended-release tablets.
- Your healthcare provider will check your diabetes with regular blood tests, including your blood sugar levels and your hemoglobin A1c.
- Low blood sugar (hypoglycemia) can happen more often when metformin hydrochloride extended-release tablets are taken with certain other diabetes medicines. Talk to your healthcare provider about how to prevent, recognize and manage low blood sugar. See “What are the possible side effects of metformin hydrochloride extended-release tablets?”
- Check your blood sugar as your healthcare provider tells you to.
- Stay on your prescribed diet and exercise program while taking metformin hydrochloride extended-release tablets.
- If you take too much metformin hydrochloride extended-release tablets, call your healthcare provider or go to the nearest hospital emergency room right away.

What should I avoid while taking metformin hydrochloride extended-release tablets?

Do not drink a lot of alcoholic drinks while taking metformin hydrochloride extended-release tablets. This means you should not binge drink for short periods, and you should not drink a lot of alcohol on a regular basis. Alcohol can increase the chance of getting lactic acidosis.

What are the possible side effects of metformin hydrochloride extended-release tablets? Metformin hydrochloride extended-release tablets may cause serious side effects, including:

- See “What is the most important information I should know about metformin hydrochloride extended-release tablets?”
- Low vitamin B12 (vitamin B12 deficiency). Using metformin hydrochloride extendedrelease tablets may cause a decrease in the amount of vitamin B12 in your blood, especially if you have had low vitamin B12 levels before. Your healthcare provider may do blood tests to check your vitamin B12 levels.
- Low blood sugar (hypoglycemia). If you take metformin hydrochloride extended-release tablets with another medicine that can cause low blood sugar, such as a sulfonylurea or insulin, your risk of getting low blood sugar is higher. The dose of your sulfonylurea medicine or insulin may need to be lowered while you take metformin hydrochloride extended-release tablets. Signs and symptoms of low blood sugar may include:
- headache
- hunger
- dizziness
- drowsiness
- fast heartbeat
- sweating
- weakness
- confusion
- irritability
- shaking or feeling jittery

Common side effects of metformin hydrochloride extended-release tablets include:

- diarrhea
- stomach-area (abdominal) pain and swelling
- nausea and vomiting
- headache
- gassiness (flatulence)
- taste disturbance (unpleasant metallic taste)
- indigestion

These are not all the possible side effects of metformin hydrochloride extended-release tablets. Call your doctor for medical advice about side effects. You may report side effects to FDA at 1-800-FDA-1088.

How should I store metformin hydrochloride extended-release tablets?

Store metformin hydrochloride extended-release tablets at room temperature between 68°F to 77°F (20°C to 25°C). See insert.

Keep bottle tightly closed between each use to protect the metformin hydrochloride extended-release tablets from moisture.

Protect from light.

Keep metformin hydrochloride extended-release tablets and all medicines out of the reach of children.

General information about the safe and effective use of metformin hydrochloride extended-release tablets

Medicines are sometimes prescribed for purposes other than those listed in a Patient Information leaflet. Do not use metformin hydrochloride extended-release tablets for a condition for which it was not prescribed. Do not give metformin hydrochloride extendedrelease tablets to other people, even if they have the same symptoms that you have. It may harm them.

You can ask your pharmacist or healthcare provider for information about metformin hydrochloride extended-release tablets that is written for health professionals.

What are the ingredients in metformin hydrochloride extended-release tablets?

Active ingredients: metformin hydrochloride.

Inactive ingredients: Povidone, Sodium Lauryl Sulfate, Magnesium Stearate, Cellulose Acetate, Polyethylene Glycol (PEG 400, PEG 8000), Triacetin, Hypromellose, Titanium Dioxide, Polysorbate 80, Ferrosoferric Oxide, Shellac.

Manufactured by:

Qingdao BAHEAL Pharmaceutical Co., Ltd.

NO.268 Yingcheng Road, Jimo, Qingdao PR China

Distributed by:

Epic Pharma LLC

Laurelton, NY 11413

Rev. 02/19